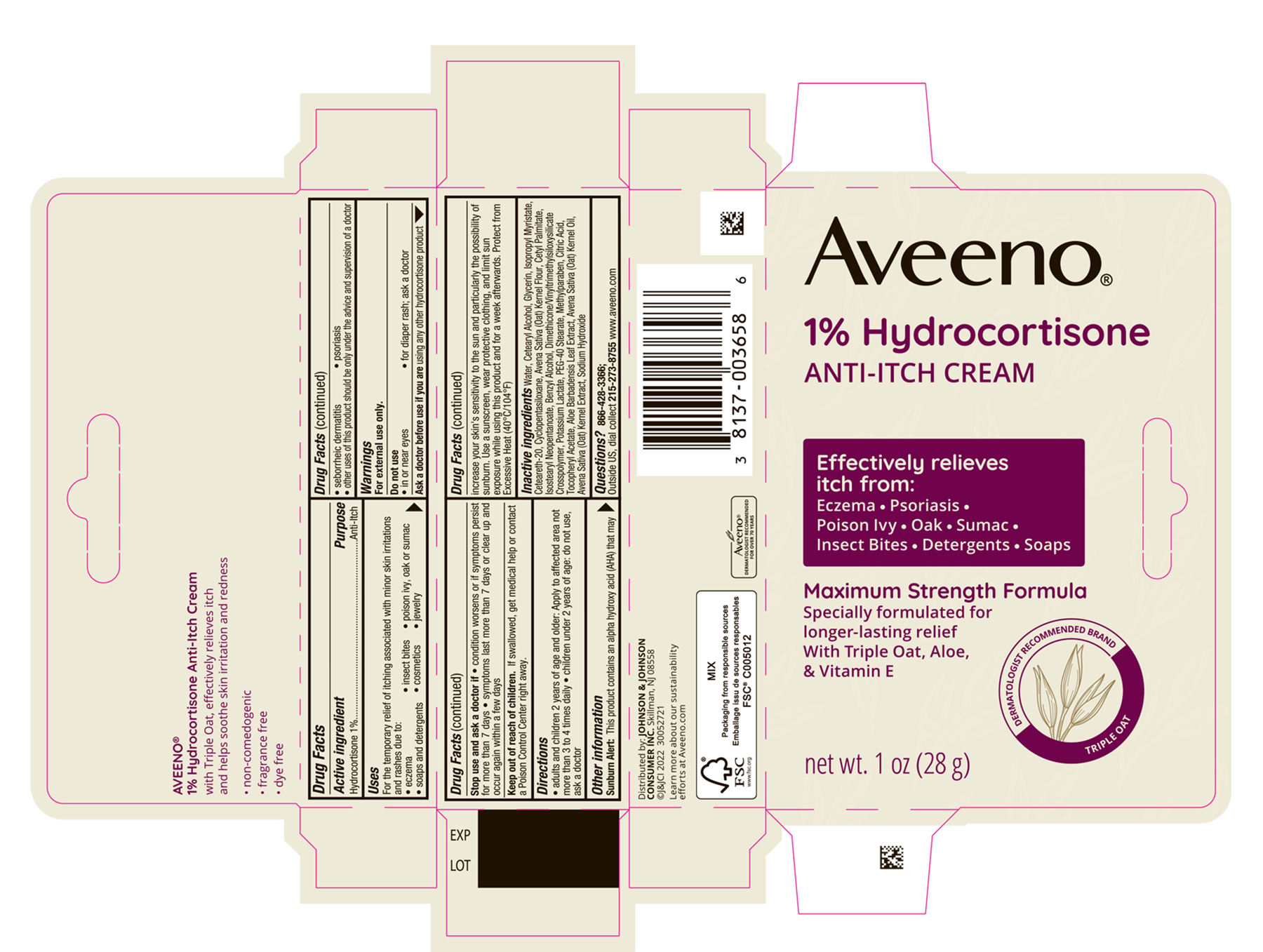 DRUG LABEL: Aveeno Hydrocortisone ANTI-ITCH
NDC: 69968-0511 | Form: CREAM
Manufacturer: Kenvue Brands LLC
Category: otc | Type: HUMAN OTC DRUG LABEL
Date: 20241105

ACTIVE INGREDIENTS: HYDROCORTISONE 10 mg/1 g
INACTIVE INGREDIENTS: WATER; CETOSTEARYL ALCOHOL; GLYCERIN; ISOPROPYL MYRISTATE; POLYOXYL 20 CETOSTEARYL ETHER; CYCLOMETHICONE 5; OATMEAL; CETYL PALMITATE; ISOSTEARYL NEOPENTANOATE; BENZYL ALCOHOL; POTASSIUM LACTATE; METHYLPARABEN; CITRIC ACID MONOHYDRATE; .ALPHA.-TOCOPHEROL ACETATE; OAT KERNEL OIL; OAT; ALOE VERA LEAF; SODIUM HYDROXIDE; PEG-40 STEARATE

Aveeno 1% Hydrocortisone ANTI-ITCH Cream

Drug Facts

Active ingredient

Hydrocortisone 1%

Purpose

Anti-Itch

Use

For the temporary relief of itching associated with minor skin irritations and rashes due to:

- eczema
- insect bites
- poison ivy, oak or sumac
- soaps and detergents
- cosmetics
- jewelry
- seborrheic dermatitis
- psoriasis
- Other uses of this product should be only under the advice and supervision of doctor

Warnings

For external use only.

Do not use

- in or near the eyes
- for diaper rash; ask a doctor

Ask a doctor before use if you are using any other hydrocortisone product

Stop use and ask a doctor if

- condition worsens or if symptoms persists for more than 7 days
- symptoms last more than 7 days or clear up and occur again within a few days

Keep out of reach of children. If swallowed, get medical help or contact a Poison Control Center right away.

Directions

- Adults and children 2 years of age and older: apply to affected area not more than 3 to 4 times daily
- children under 2 years of age, do not use; ask a doctor.

Sunburn Alert

This product contains an alpha hydroxy acid (AHA) that may increase your skin's sensitivity to the sun and particularly the possibility of sunburn. Use a sunscreen, wear protective clothing, and limit sun exposure while using this product and for a week afterwards.

Other information

Protect from Excessive Heat (40°c/104°F)

Inactive ingredients

Water, Cetearyl Alcohol, Glycerin, Isopropyl Myristate, Cetereath-20, Cyclopentasiloxane, Avena Sativa (Oat) Kernel flour, Cetyl Palmitate, Isostearyl Neopentanoate, Benzyl Alcohol, Dimethicone/Vinyltrimethylsiloxysilicate Crosspolymer, Potassium Lactate, PEG-40 Stearate, Methylparaben, Citric Acid, Tocopheryl Acetate, Aloe Barbadensis Leaf Extract, Avena Sativa (Oat) Kernel Oil, Avena Sativa (Oat) Kernel Extract, Sodium Hydroxide

Questions?

866-428-3366; Outside US, dial collect 215-273-8755 www.aveeno.com

Distributed by:
JOHNSON & JOHNSON CONSUMER INC.
Skillman, NJ 08558

PRINCIPAL DISPLAY PANEL - 28 g Tube Carton

Aveeno®

1% Hydrocortisone

ANTI-ITCH CREAM

Effectively relieves itch from:

Eczema ● Psoriasis

Poison Ivy ● Oak ● Sumac

Insect Bites ● Detergents ● Soaps

Maximum Strength Formula

Specially formulated for longer-lasting relief

With Triple Oat, Aloe, & Vitamin E

DERMATOLOGIST RECOMMENDED BRAND

TRIPLE OAT

net wt. 1 oz (28 g)